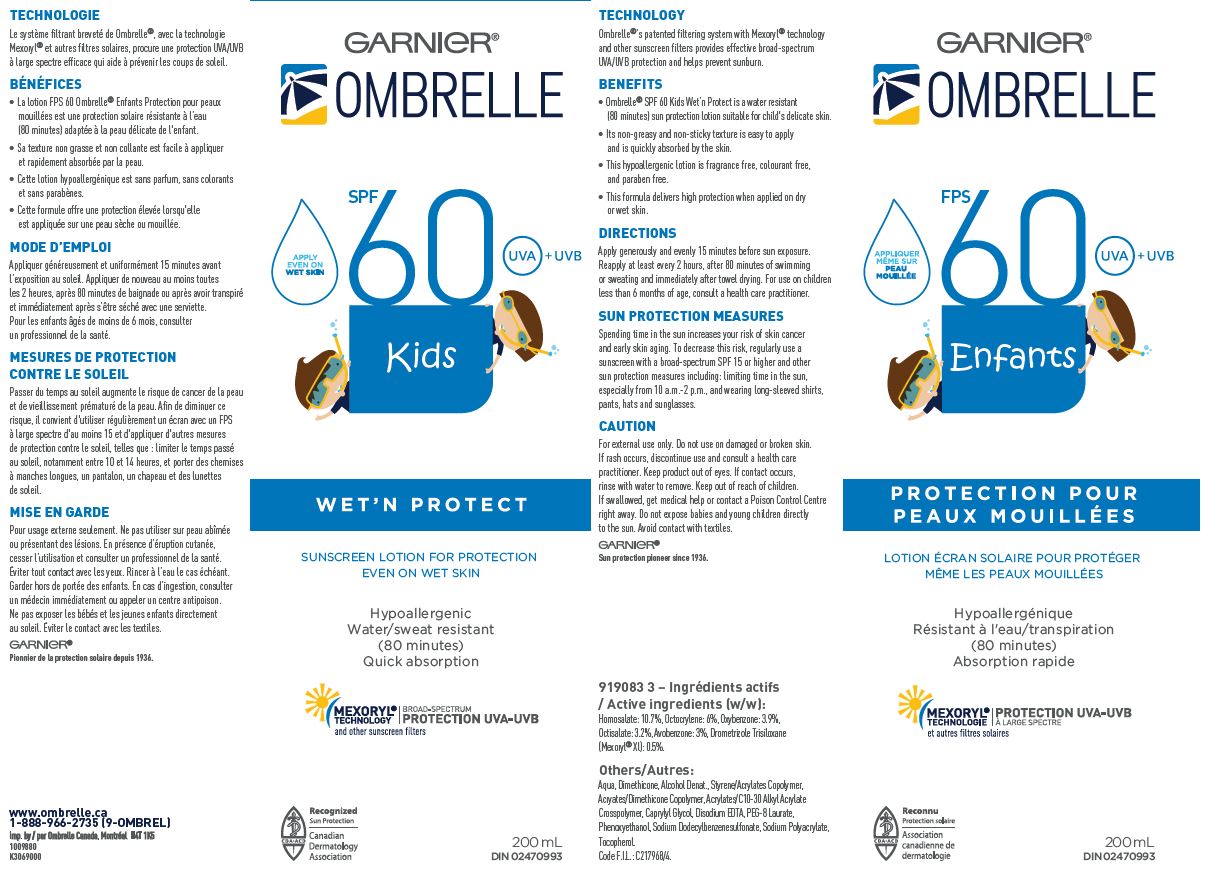 DRUG LABEL: Garnier Ombrelle SPF 60 UVA UVB Kids Wet N Protect Sunscreen Protection Even on Wet Skin Hypoallergenic Water/sweat resistant 80 minutes Quick Absorption
NDC: 49967-704 | Form: LOTION
Manufacturer: L'Oreal USA Products Inc
Category: prescription | Type: HUMAN PRESCRIPTION DRUG LABEL
Date: 20260107

ACTIVE INGREDIENTS: HOMOSALATE 107 mg/1 mL; OCTOCRYLENE 60 mg/1 mL; OXYBENZONE 39 mg/1 mL; OCTISALATE 32 mg/1 mL; AVOBENZONE 30 mg/1 mL; DROMETRIZOLE TRISILOXANE 5 mg/1 mL
INACTIVE INGREDIENTS: WATER; DIMETHICONE; ALCOHOL; CAPRYLYL GLYCOL; EDETATE DISODIUM; PEG-8 LAURATE; PHENOXYETHANOL; SODIUM DODECYLBENZENESULFONATE; SODIUM POLYACRYLATE (8000 MW); TOCOPHEROL

Drug Facts

Active ingredients

Homosalate 10.7%
Octocrylene 6%
Oxybenzone 3.9%
Octisalate 3.2%
Avobenzone 3%
Drometrizole Trisiloxane 0.5%

Others

Aqua, Alcohol Denat., Dimethicone, Styrene/Acrylates Copolymer, Acrylates/Dimethicone Copolymer, Acrylates/C10-30 Alkyl Acrylate Crosspolymer, Caprylyl Glycol, Disodium EDTA, PEG-8 Laurate, Phenoxyethanol, Sodium Dodecylbenzenesulfonate, Sodium Polyacrylate, Tocopherol

Technology

Ombrelle’s patented filtering system with Mexoryl technology and other sunscreen filters provides effective broad-spectrum UVA/UVB protection and helps prevent sunburns.

Direction

Apply generously and evenly 15 minutes before sun exposure. Reapply at least every 2 hours, after 80 minutes of swimming or sweating and immediately after towel drying. For use on children less than 6 months of age, consult a health care practitioner.

SUN PROTECTION MEASURES
Spending time in the sun increases your risk of skin cancer and early skin aging. To decrease this risk, regularly use a sunscreen with a Broad Spectrum SPF value of 15 or higher and other sun protection measures including: limiting time in the sun, especially from 10 a.m. – 2 p.m., and wearing long-sleeved shirts, pants, hats, and sunglasses.

Caution

For external use only. Do not use on damaged or broken skin. If rash occurs, discontinue use and consult a health care practitioner. Keep product out of eyes. IF contact occurs, rinse with water to remove. Keep out of reach of children. If swallowed, get medical help or contact a Poison Control Centre right away. Do not expose babies and young children directly to the sun. Avoid contact with textiles.